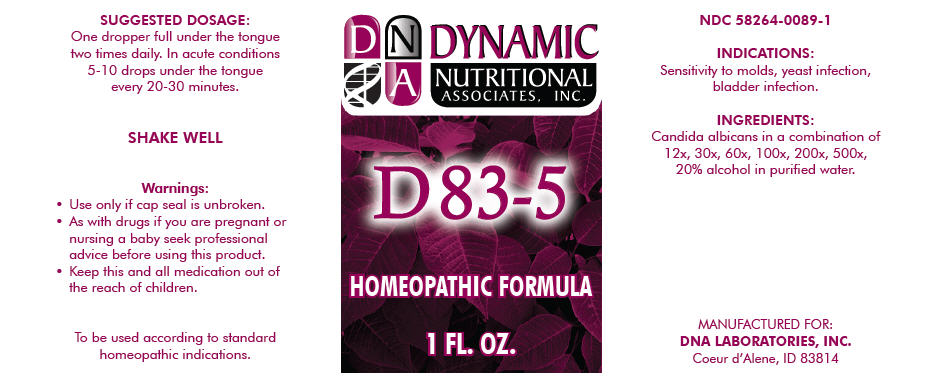 DRUG LABEL: D83-5
NDC: 58264-0089 | Form: SOLUTION
Manufacturer: DNA Labs, Inc.
Category: homeopathic | Type: HUMAN OTC DRUG LABEL
Date: 20250113

ACTIVE INGREDIENTS: CANDIDA ALBICANS 500 [hp_X]/1 mL
INACTIVE INGREDIENTS: ALCOHOL; WATER

D83-5

NDC 58264-0089-1

INDICATIONS AND USAGE

INDICATIONS

Sensitivity to molds, yeast infection, bladder infection.

ACTIVE INGREDIENT

INGREDIENTS

Candida albicans in a combination of 12x, 30x, 60x, 100x, 200x, 500x, 20% alcohol in purified water.

SUGGESTED DOSAGE

One dropper full under the tongue two times daily. In acute conditions 5-10 drops under the tongue every 20-30 minutes.

STORAGE AND HANDLING

SHAKE WELL

Warnings

- Use only if cap seal is unbroken.

PREGNANCY OR BREAST FEEDING

- As with drugs if you are pregnant or nursing a baby seek professional advice before using this product.

KEEP OUT OF REACH OF CHILDREN

- Keep this and all medication out of the reach of children.

To be used according to standard homeopathic indications.

PRINCIPAL DISPLAY PANEL - 1 FL. OZ. Bottle Label

DYNAMIC
NUTRITIONAL
ASSOCIATES, INC.

D 83-5

HOMEOPATHIC FORMULA

1 FL. OZ.